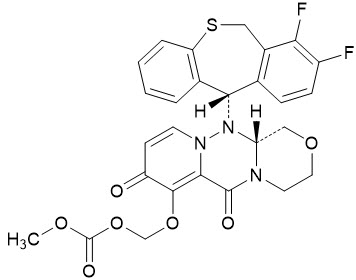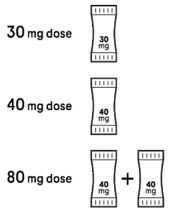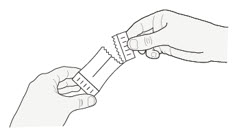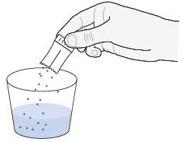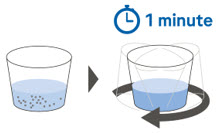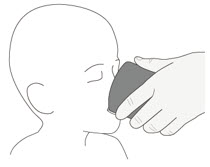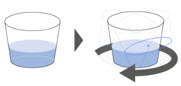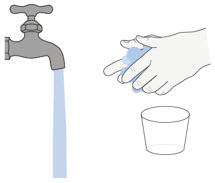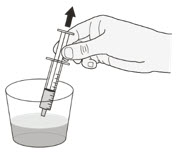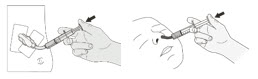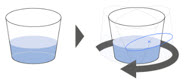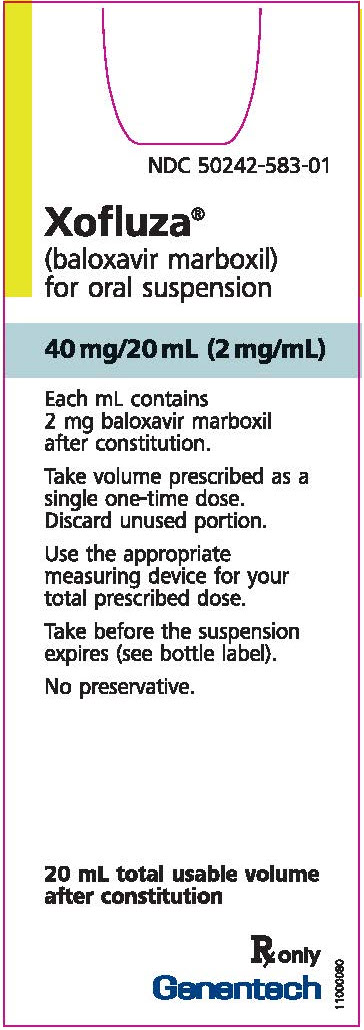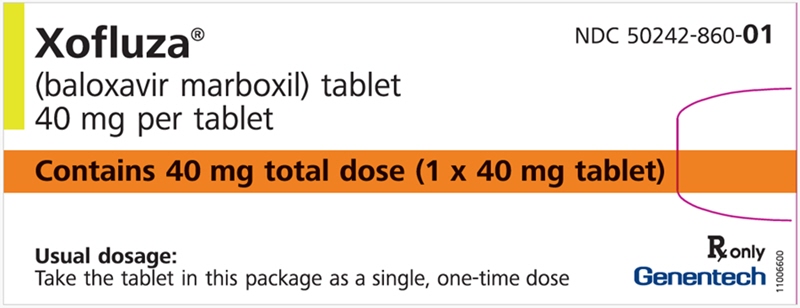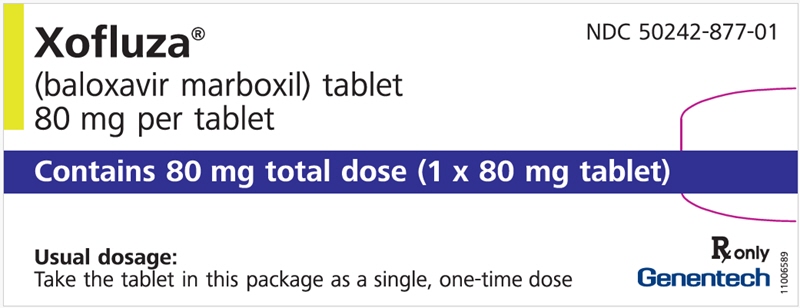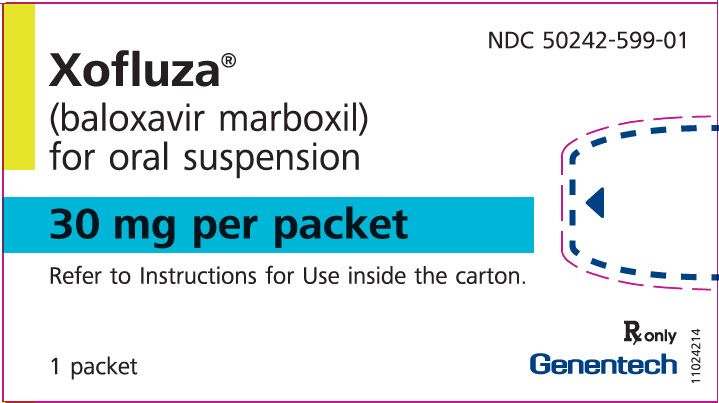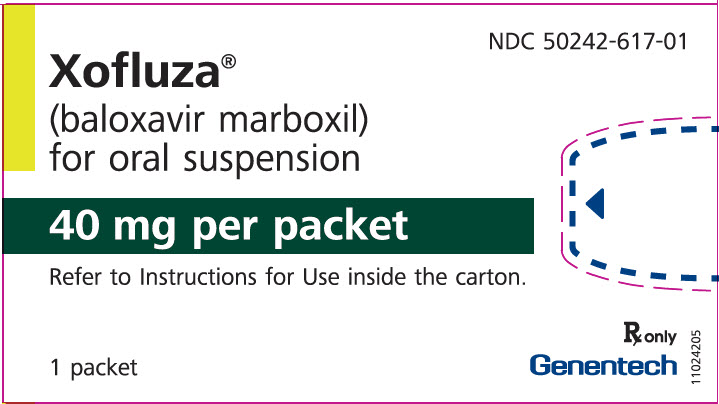 DRUG LABEL: Xofluza
NDC: 50242-860 | Form: TABLET, FILM COATED
Manufacturer: Genentech, Inc.
Category: prescription | Type: HUMAN PRESCRIPTION DRUG LABEL
Date: 20251215

ACTIVE INGREDIENTS: BALOXAVIR MARBOXIL 40 mg/1 1
INACTIVE INGREDIENTS: LACTOSE MONOHYDRATE; CROSCARMELLOSE SODIUM; POVIDONE K25; MICROCRYSTALLINE CELLULOSE; SODIUM STEARYL FUMARATE; HYPROMELLOSE, UNSPECIFIED; TALC; TITANIUM DIOXIDE

HIGHLIGHTS OF PRESCRIBING INFORMATION

These highlights do not include all the information needed to use XOFLUZA safely and effectively. See full prescribing information for XOFLUZA.
XOFLUZA® (baloxavir marboxil) tablets, for oral use
XOFLUZA® (baloxavir marboxil) for oral suspension
Initial U.S. Approval: 2018

RECENT MAJOR CHANGES

Dosage and Administration (2.1, 2.2, 2.3, 2.4) | 05/2025

1 INDICATIONS AND USAGE

XOFLUZA is an influenza virus polymerase acidic (PA) endonuclease inhibitor indicated for:

- Treatment of acute uncomplicated influenza in patients 5 years of age and older who have been symptomatic for no more than 48 hours and who are otherwise healthy or at high risk of developing influenza-related complications. (1.1)
- Post-exposure prophylaxis of influenza in patients 5 years of age and older following contact with an individual who has influenza. (1.2)

Limitations of Use

Influenza viruses change over time, and factors such as the virus type or subtype, emergence of resistance, or changes in viral virulence could diminish the clinical benefit of antiviral drugs. Consider available information on drug susceptibility patterns for circulating influenza virus strains when deciding whether to use XOFLUZA. (1.3)

2 DOSAGE AND ADMINISTRATION

Treatment and Post-Exposure Prophylaxis of Influenza

- Take XOFLUZA as a single dose as soon as possible and within 48 hours of influenza symptom onset for treatment of acute uncomplicated influenza or following contact with an individual who has influenza. XOFLUZA may be taken with or without food. (2.1, 2.2)

Patient Body Weight | Recommended Single Oral Dose in Patients 5 Years of Age and Older (Tablets)
20 kg to less than 80 kg | One 40 mg tablet (blister card contains one 40 mg tablet)
At least 80 kg | One 80 mg tablet (blister card contains one 80 mg tablet)

Patient Body Weight | Recommended Single Oral Dose in Patients 5 Years of Age and Older For Oral Suspension (Packets)
15 kg to less than 20 kg | One 30 mg packet
20 kg to less than 80 kg | One 40 mg packet
At least 80 kg | 80 mg (two 40 mg packets)

Patient Body Weight | Recommended Single Oral Dose in Patients 5 Years of Age and Older For Oral Suspension (Bottles)
Less than 20 kg | 2 mg/kg
20 kg to less than 80 kg | 40 mg (20 mL)
At least 80 kg | 80 mg (40 mL)

Refer to the Full Prescribing Information for additional information on the recommended dosage and preparation of XOFLUZA for oral suspension (bottles) or for oral suspension (packets) for both for oral or enteral use in patients 5 years of age and older. (2.2, 2.3)

3 DOSAGE FORMS AND STRENGTHS

- Tablets: 40 mg and 80 mg. (3)
- For oral suspension (packets): 30 mg and 40 mg per packet in about 15-20 mL of drinking water. (3)
- For oral suspension (bottles): 40 mg/20 mL (2 mg/mL) after reconstitution. (3).

4 CONTRAINDICATIONS

XOFLUZA is contraindicated in patients with a history of hypersensitivity to baloxavir marboxil or any of its ingredients. (4)

5 WARNINGS AND PRECAUTIONS

- Hypersensitivity such as anaphylaxis, angioedema, urticaria, and erythema multiforme: Initiate appropriate treatment if an allergic-like reaction occurs or is suspected. (5.1)
- Increased incidence of Treatment-Emergent Resistance in Patients Less Than 5 Years of Age: XOFLUZA is not indicated in patients less than 5 years of age due to increased incidence of treatment-emergent resistance in this age group. In clinical trials, incidence of virus with treatment-emergent substitutions associated with reduced susceptibility to baloxavir (resistance) was higher in pediatric subjects younger than 5 years of age than older subjects. (5.2)
- Risk of bacterial infection: Serious bacterial infections may begin with influenza-like symptoms or may coexist with, or occur as, a complication of influenza. XOFLUZA has not been shown to prevent such complications. Prescribers should be alert to potential secondary bacterial infections and treat them as appropriate. (5.3)

6 ADVERSE REACTIONS

Adverse events reported in at least 1% of adult and adolescent influenza subjects treated with XOFLUZA included diarrhea (3%), bronchitis (3%), nausea (2%), sinusitis (2%), and headache (1%). (6.1)

Adverse events reported in at least 5% of pediatric subjects (5 to < 12 years) treated with XOFLUZA included vomiting (5%) and diarrhea (5%).

To report SUSPECTED ADVERSE REACTIONS, contact Genentech at 1-888-835-2555 or FDA at 1-800-FDA-1088 or www.fda.gov/medwatch.

7 DRUG INTERACTIONS

- Avoid coadministration of XOFLUZA with dairy products, calcium-fortified beverages, polyvalent cation-containing laxatives, antacids, or oral supplements (e.g., calcium, iron, magnesium, selenium, or zinc). (2.1,7.1)
- Live attenuated influenza vaccines may be affected by antivirals. (7.2)

FULL PRESCRIBING INFORMATION

1 INDICATIONS AND USAGE

1.1 Treatment of Influenza

XOFLUZA is indicated for treatment of acute uncomplicated influenza in patients 5 years of age and older who have been symptomatic for no more than 48 hours and who are otherwise healthy or at high risk of developing influenza-related complications^1 [see Clinical Studies (14.1, 14.2, and 14.3].

1.2 Post-Exposure Prophylaxis of Influenza

XOFLUZA is indicated for post-exposure prophylaxis of influenza in persons 5 years of age and older following contact with an individual who has influenza [see Clinical Studies (14.4)].

1.3 Limitations of Use

Influenza viruses change over time, and factors such as the virus type or subtype, emergence of resistance, or changes in viral virulence could diminish the clinical benefit of antiviral drugs. Consider available information on drug susceptibility patterns for circulating influenza virus strains when deciding whether to use XOFLUZA [see Warnings and Precautions (5.2), Microbiology (12.4) and Clinical Studies (14)].

2 DOSAGE AND ADMINISTRATION

2.1 Dosage and Administration Overview

XOFLUZA is available in two dosage forms:

- XOFLUZA tablets (40 mg and 80 mg).
- XOFLUZA for oral suspension is available in two different presentations: packets (30 mg and 40 mg) and bottles (2 mg/mL). If the patient weighs less than 15 kg, XOFLUZA for oral suspension in bottle is the recommended presentation. Both presentations of the for oral suspension are intended for patients who are unable to or have difficulty swallowing tablets, or those who require enteral administration [see Dosage and Administration (2.2, 2.3, 2.4)].

Take XOFLUZA as soon as possible after influenza symptom onset or exposure to influenza [see Dosage and Administration (2.2)].

XOFLUZA may be taken with or without food. However, concomitant use of XOFLUZA with dairy products, calcium-fortified beverages, polyvalent cation-containing laxatives, antacids, or oral supplements (e.g., calcium, iron, magnesium, selenium, or zinc) should be avoided [see Drug Interactions (7.1) and Clinical Pharmacology (12.3)].

2.2 Recommended Dosage

Treatment of Acute Uncomplicated Influenza or Post-Exposure Prophylaxis in Adults, and Pediatric Patients (5 Years of Age and Older)

Take XOFLUZA as a single dose as soon as possible and within 48 hours of influenza symptom onset for treatment of acute uncomplicated influenza or following contact with an individual who has influenza. The recommended dosage of XOFLUZA in patients 5 years of age or older is a single weight-based dose displayed in Tables 1, 2 and 3.

Table 1 XOFLUZA Tablets: Recommended Dosage in Adults and Pediatric Patients 5 Years of Age and Older
Patient Body Weight | Recommended Single Oral Dose (Tablets) [Recommended XOFLUZA dosage is based on the patient's weight.]
20 kg to less than 80 kg | One 40 mg tablet (blister card contains one 40 mg tablet)
At least 80 kg | One 80 mg tablet (blister card contains one 80 mg tablet)

Table 2 XOFLUZA for Oral Suspension (Packets): Recommended Dosage in Adults and Pediatric Patients 5 Years of Age and Older
Patient Body Weight | Recommended Single Oral Dose (Packets) [Recommended XOFLUZA dosage is based on the patient's weight.]
15 kg [Patients who weigh less than 15 kg should receive XOFLUZA for oral suspension (bottles).] to less than 20 kg | One 30 mg packet
20 kg to less than 80 kg | One 40 mg packet
At least 80 kg | 80 mg (two 40 mg packets)

Table 3 XOFLUZA for Oral Suspension (Bottles): Recommended Dosage in Adults and Pediatric Patients 5 Years of Age and Older
Patient Body Weight | Recommended Single Oral Dose [Recommended XOFLUZA dosage is based on the patient's weight.] , [Use a measuring device (oral syringe) to measure the prescribed dose for use.] (For Oral Suspension in Bottles)
Less than 20 kg | 2 mg/kg
20 kg to less than 80 kg | 40 mg (20 mL)
At least 80 kg | 80 mg (40 mL [Dosage requires two bottles of XOFLUZA for oral suspension.])

2.3 Preparation of XOFLUZA for Oral Suspension (Packets) by Patient or Caregiver

See the XOFLUZA for oral suspension (packets) Instructions for Use for details on the preparation and administration (oral or via enteral feeding tube).

- For the 30 mg or 40 mg dose, mix in a small container with 1 tablespoon (about 15-20 mL) of room temperature drinking water. Once the supplied XOFLUZA for oral suspension (packets) have fully dispersed in the drinking water, take the entire mixture immediately.
- For the 80 mg dose, use two 40 mg packets. Prepare each packet as described above for the 40 mg dose and take the packets separately.
- For enteral administration (i.e., feeding tube), draw up the entire contents with an enteral syringe and administer through a tube that is 4 French or larger. Flush with 1 mL of water before and after enteral administration.

2.4 Preparation of XOFLUZA for Oral Suspension (Bottles) by Healthcare Provider

Prior to dispensing to the patient, reconstitute XOFLUZA for oral suspension (bottles) with 20 mL of drinking water or sterile water. After reconstitution, each bottle of XOFLUZA for oral suspension (bottles) contains 40 mg of baloxavir marboxil per 20 mL of volume for a final concentration of 2 mg/mL. The for oral suspension (bottles) can be used for oral or enteral use. Only take the contents of the full bottle(s) of XOFLUZA for oral suspension (bottles) with the use of a measuring device (oral syringe). Ensure the caregiver or patient uses an oral syringe to measure the prescribed dose of XOFLUZA for oral suspension (bottles). Patients may need to draw up XOFLUZA for oral suspension (bottles) multiple times using the oral syringe to receive the full dose.

Reconstituting XOFLUZA for Oral Suspension (Bottles)

Prepare the for oral suspension (bottles) at the time of dispensing. Administration must occur within 10 hours after reconstitution because this product does not contain a preservative.

1. Gently tap the bottom of the bottle to loosen the granules.
2. Reconstitute XOFLUZA for oral suspension (bottles) with 20 mL of drinking water or sterile water.
3. Gently swirl the suspension to ensure that the granules are evenly suspended. Do not shake.
4. Write the expiration time and date on the bottle label in the space provided (10 hours from reconstitution time).

Important Information for the Healthcare Provider

- Provide caregiver or patient with a measuring device (oral syringe) to deliver the prescribed dose of the for suspension for oral use (bottles). For enteral administration (i.e., feeding tube), draw up for oral suspension (bottles) with an enteral syringe and administer through a tube that is 4 French or larger. Flush with 1 mL of water before and after enteral administration.
- Instruct the caregiver or patient that the total prescribed dose of XOFLUZA for oral suspension (bottles) may require:
  - Less than one bottle (e.g., for pediatric patients 5 years of age and older who weigh less than 20 kg)
  - One bottle (e.g., for adults and adolescents weighing 20 kg to less than 80 kg), or
  - Two bottles (e.g., for adults and adolescents weighing at least 80 kg).

3 DOSAGE FORMS AND STRENGTHS

XOFLUZA Tablets:

- 40 mg: white to light yellow, oblong-shaped, film-coated, debossed with "BXM40" on one side.
- 80 mg: white to light yellow, oblong shaped, film-coated, debossed with "BXM80" on one side.

XOFLUZA for Oral Suspension (Packets):

- 30 mg: white to light yellow granules with strawberry flavor (each packet contains 30 mg baloxavir marboxil).
- 40 mg: white to light yellow granules with strawberry flavor (each packet contains 40 mg baloxavir marboxil).

XOFLUZA for Oral Suspension (Bottles):

- 40 mg/20 mL (2 mg/mL) of baloxavir marboxil after reconstitution with 20 mL of drinking water or sterile water. The granules are white to light yellow. The reconstituted product is a greyish white, white to light yellow opaque suspension with strawberry flavor.

4 CONTRAINDICATIONS

XOFLUZA is contraindicated in patients with a history of hypersensitivity to baloxavir marboxil or any of its ingredients. Serious allergic reactions have included anaphylaxis, angioedema, urticaria, and erythema multiforme [see Warnings and Precautions (5.1)].

5 WARNINGS AND PRECAUTIONS

5.1 Hypersensitivity

Cases of anaphylaxis, urticaria, angioedema, and erythema multiforme have been reported in postmarketing experience with XOFLUZA. Appropriate treatment should be instituted if an allergic-like reaction occurs or is suspected. The use of XOFLUZA is contraindicated in patients with known hypersensitivity to XOFLUZA [see Contraindications (4) and Adverse Reactions (6.2)].

5.2 Increased Incidence of Treatment-Emergent Resistance in Patients Less Than 5 Years of Age

XOFLUZA is not indicated in patients less than 5 years of age due to increased incidence of treatment-emergent resistance in this age group. In clinical trials, the incidence of virus with treatment-emergent substitutions associated with reduced susceptibility to baloxavir (resistance) was higher in pediatric subjects younger than 5 years of age (40%, 38/96) than in pediatric subjects ≥ 5 years to < 12 years of age (16%, 19/117) or subjects ≥ 12 years of age (7%, 60/842). The potential for transmission of resistant strains in the community has not been determined [see Indications and Usage (1), Use in Specific Populations (8.4), and Microbiology (12.4)].

5.3 Risk of Bacterial Infections

There is no evidence of efficacy of XOFLUZA in any illness caused by pathogens other than influenza viruses. Serious bacterial infections may begin with influenza-like symptoms or may coexist with, or occur as, a complication of influenza. XOFLUZA has not been shown to prevent such complications. Prescribers should be alert to potential secondary bacterial infections and treat them as appropriate.

6 ADVERSE REACTIONS

6.1 Clinical Trials Experience

Because clinical trials are conducted under widely varying conditions, adverse reaction rates observed in the clinical trials of a drug cannot be directly compared to rates in the clinical trials of another drug and may not reflect the rates observed in practice.

The overall safety profile of XOFLUZA is based on data from 2,079 subjects, 5 years of age and older in 5 controlled clinical trials who received XOFLUZA. Of these subjects, 1,943 were adults and adolescents (≥ 12 years of age) and 136 were in the pediatric age group (5 to < 12 years of age) [see Clinical Studies (14)].

Treatment of Acute Uncomplicated Influenza

Adult and Adolescent Subjects (≥ 12 Years of Age):

The safety of XOFLUZA in adult and adolescent subjects is based on data from 3 placebo-controlled trials in which a total of 1,640 subjects received XOFLUZA: 1,334 (81%) subjects were 18 to 64 years of age, 209 (13%) subjects were adults 65 years of age or older, and 97 (6%) subjects were adolescents 12 to 17 years of age. These trials included otherwise healthy adults and adolescents (N=910) and subjects at high risk of developing complications associated with influenza (N=730). Of these, 1,440 subjects received XOFLUZA at the recommended dose [see Clinical Studies (14.1, 14.2)]. Trial T0821 was a phase 2 dose-finding placebo-controlled trial where otherwise healthy adult subjects 20 to 64 years of age received single oral dose of XOFLUZA or placebo. Trial T0831 was a placebo- and active-controlled trial in otherwise healthy adults and adolescents 12 to 64 years of age; subjects received weight-based XOFLUZA or placebo as a single oral dose on Day 1 or oseltamivir twice a day for 5 days. Trial T0832 was a randomized, double-blind, placebo- and active-controlled trial where adults and adolescents at high risk of influenza complications 12 years of age and older received either XOFLUZA, placebo or oseltamivir.

Table 4 displays the most common adverse events (regardless of causality assessment) reported in at least 1% of adult and adolescent subjects who received XOFLUZA at the recommended dose in Trials T0821, T0831, and T0832.

Table 4 Incidence of Adverse Events Occurring in at Least 1% of Adult and Adolescent Subjects Receiving XOFLUZA in the Acute Uncomplicated Influenza Trials T0821, T0831, and T0832
Adverse Event | XOFLUZA (N=1,440) | Placebo (N=1,136)
Diarrhea | 3% | 4%
Bronchitis | 3% | 4%
Nausea | 2% | 3%
Sinusitis | 2% | 3%
Headache | 1% | 1%

Pediatric Subjects (5 to < 12 Years of Age):

In an active-controlled, double-blind trial Trial CP40563 in pediatric subjects, a total of 79 subjects 5 to less than 12 years of age, received the recommended weight-based dosage of XOFLUZA, and 39 subjects received oseltamivir. Of the 118 subjects 5 to less than 12 years of age in Trial CP40563, 15 subjects in the XOFLUZA arm and 4 subjects in the oseltamivir arm were at high risk of developing influenza complications. The most frequently reported AEs (≥ 5%) in all subjects in the XOFLUZA treatment arm were vomiting (5%) and diarrhea (5%). Vomiting was reported in 18% of subjects in the oseltamivir arm [see Clinical Studies (14.3]. There are limited safety data in patients 5 to <12 years at high risk of developing influenza complications.

Post-Exposure Prophylaxis of Influenza

In a placebo-controlled clinical trial, Trial T0834, conducted in adults, and pediatric subjects ≥ 5 years of age, a total of 360 subjects received XOFLUZA, of which 291 (81%) were adults ≥ 18 years; 12 (3%) subjects were adolescents ≥ 12 to 17 years and 57 (16%) were pediatric subjects 5 to < 12 years of age. The safety profile was similar in pediatric patients aged 5 to < 12 years old as that reported in adults and adolescents 12 years of age and older [see Clinical Studies (14.4)].

6.2 Postmarketing Experience

The following adverse reactions have been identified during postmarketing use of XOFLUZA. Because these reactions are reported voluntarily from a population of uncertain size, it is not possible to reliably estimate their frequency or establish a causal relationship to XOFLUZA exposure.

Immune System Disorders: Anaphylactic reactions, anaphylactic shock, anaphylactoid reactions, hypersensitivity reactions, angioedema (swelling of face, eyelids, tongue and lips)

Skin and Subcutaneous Tissue Disorders: Rash, urticaria, erythema multiforme

Gastrointestinal Disorders: Vomiting, hematochezia, melena, colitis

Psychiatric Disorders: Delirium, abnormal behavior, hallucinations

7 DRUG INTERACTIONS

7.1 Effect of Other Drugs on XOFLUZA

Baloxavir may form a chelate with polyvalent cations such as calcium, aluminum, or magnesium. Coadministration with polyvalent cation-containing products may decrease plasma concentrations of baloxavir [see Clinical Pharmacology (12.3)], which may reduce XOFLUZA efficacy. Avoid coadministration of XOFLUZA with dairy products, calcium-fortified beverages, polyvalent cation-containing laxatives, antacids, or oral supplements (e.g., calcium, iron, magnesium, selenium, or zinc).

7.2 Vaccines

The concurrent use of XOFLUZA with intranasal live attenuated influenza vaccine (LAIV) has not been evaluated. Concurrent administration of antiviral drugs may inhibit viral replication of LAIV and thereby decrease the effectiveness of LAIV vaccination. Interactions between inactivated influenza vaccines and XOFLUZA have not been evaluated.

8 USE IN SPECIFIC POPULATIONS

8.1 Pregnancy

Risk Summary

There are no adequate and well-controlled studies with XOFLUZA in pregnant women to inform a drug-associated risk of adverse developmental outcomes. There are risks to the mother and fetus associated with influenza virus infection in pregnancy (see Clinical Considerations). In animal reproduction studies, no adverse developmental effects were observed in rats or rabbits with oral administration of baloxavir marboxil at exposures approximately 5 (rats) and 7 (rabbits) times the systemic baloxavir exposure at the maximum recommended human dose (MRHD) (see Data).

The estimated background risk of major birth defects and miscarriage for the indicated population is unknown. All pregnancies have a background risk of birth defects, loss, or other adverse outcomes. In the U.S. general population, the estimated background risk of major birth defects and miscarriage in clinically recognized pregnancies is 2%–4% and 15%–20%, respectively.

Clinical Considerations

Disease-Associated Maternal and/or Embryo/Fetal Risk

Pregnant women are at higher risk of severe complications from influenza, which may lead to adverse pregnancy and/or fetal outcomes, including maternal death, stillbirth, birth defects, preterm delivery, low birth weight, and small for gestational age.

Data

Animal Data

Baloxavir marboxil was administered orally to pregnant rats (20, 200, or 1,000 mg/kg/day from gestation day 6 to 17) and rabbits (30, 100, or 1,000 mg/kg/day from gestation day 7 to 19). No adverse embryo-fetal effects were observed in rats up to the highest dose of baloxavir marboxil (1,000 mg/kg/day), resulting in systemic baloxavir exposure (AUC) of approximately 5 times the exposure at the MRHD. In rabbits, fetal skeletal variations occurred at a maternally toxic dose (1,000 mg/kg/day) resulting in 2 abortions out of 19 pregnancies. No adverse maternal or embryo-fetal effects were observed in rabbits at the middle dose (100 mg/kg/day) resulting in systemic baloxavir exposure (AUC) approximately 7 times the exposure at the MRHD.

In the prenatal and postnatal development study in rats, baloxavir marboxil was administered orally at 20, 200, or 1,000 mg/kg/day from gestation day 6 to postpartum/lactation day 20. No significant effects were observed in the offspring at maternal systemic baloxavir exposure (AUC) approximately 5 times the exposure at the MRHD.

8.2 Lactation

Risk Summary

There are no data on the presence of baloxavir marboxil in human milk, the effects on the breastfed infant, or the effects on milk production. Baloxavir and its related metabolites were present in the milk of lactating rats (see Data). The developmental and health benefits of breastfeeding should be considered along with the mother's clinical need for XOFLUZA and any potential adverse effects on the breastfed child from the drug or from the underlying maternal condition.

Data

In a lactation study, baloxavir and its related metabolites were excreted in the milk of lactating rats administered baloxavir marboxil (1 mg/kg) on postpartum/lactation day 11, with peak milk concentration approximately 5 times that of maternal plasma concentrations occurring 2 hours post-dose. No effects of baloxavir marboxil on growth and postnatal development were observed in nursing pups at the highest oral dose tested in rats. Maternal systemic exposure was approximately 5 times the baloxavir exposure in humans at the MRHD.

8.4 Pediatric Use

Treatment of Acute Uncomplicated Influenza in Adolescent Subjects (≥ 12 Years of Age)

The safety and effectiveness of XOFLUZA for the treatment of acute uncomplicated influenza in adolescent subjects 12 years of age and older weighing at least 40 kg is supported by one randomized, double-blind, controlled trial in otherwise healthy subjects Trial T0831 and one trial in subjects at high risk of developing influenza-related complications Trial T0832 [see Clinical Studies (14.1)]. A total of 117 otherwise healthy adolescents 12 to17 years of age were randomized and received either XOFLUZA (N=76) or placebo (N=41) in Trial T0831; 38 adolescents 12 to 17 years of age at high risk for influenza complications were randomized and received either XOFLUZA (N=21) or placebo (N=17) in Trial T0832. The median time to alleviation of symptoms in influenza-infected adolescent subjects aged 12 to 17 years in Trial T0831 was comparable to that observed in adults. In Trial T0832, the median time to improvement of symptoms in the limited number of influenza-infected adolescent subjects aged 12 to 17 years was similar in the XOFLUZA and placebo arms [see Clinical Studies (14.1)]. Adverse events reported in adolescents in both trials were similar to those reported in adults [see Adverse Reactions (6.1)].

Treatment of Acute Uncomplicated Influenza in Pediatric Subjects (5 to < 12 Years of Age)

The safety and effectiveness of XOFLUZA in pediatric subjects 5 to less than 12 years of age is supported by one randomized, double-blind, controlled trial Trial CP40563 with a primary endpoint of safety. In this trial, 118 pediatric subjects were randomized and treated in a 2:1 ratio and received either XOFLUZA (N=79) or oseltamivir (N=39). Efficacy was extrapolated from adults and adolescents based on comparable PK exposures in adults, adolescents and pediatric subjects 5 to less than 12 years of age. The median time to alleviation of signs and symptoms in influenza-infected subjects was comparable in the XOFLUZA and oseltamivir arms. Adverse events reported with XOFLUZA in pediatric subjects were similar to those observed in adults and adolescents except for vomiting and diarrhea, which were both more commonly reported in pediatric subjects [see Adverse Reactions (6.1), Clinical Pharmacology (12.3), and Clinical Studies (14.1)].

Post-Exposure Prophylaxis of Influenza in Pediatric and Adolescent Subjects (5 to < 18 Years of Age)

The safety and effectiveness of XOFLUZA for post-exposure prophylaxis in pediatric and adolescent subjects 5 to less than 18 years of age is supported by one randomized, double-blind, controlled trial conducted in Japan Trial T0834 [see Clinical Studies (14.3)]. Subjects in this trial were randomized in a 1:1 ratio to receive XOFLUZA or placebo. A total of 69 subjects from 5 to <18 years of age in Trial T0834 received XOFLUZA. The incidence of RT-PCR-confirmed symptomatic influenza in pediatric subjects 5 to <18 years of age was similar to that observed in adult subjects [see Clinical Pharmacology (12.3), and Clinical Studies (14.3)]. Efficacy was extrapolated from adults based on comparable PK exposures in adults, adolescents and pediatric subjects 5 to <18 years of age.

Adverse events reported in pediatric and adolescent subjects were similar to those reported in adults in the same trial [see Adverse Reactions (6.1)].

Pediatric Subjects (< 5 Years of Age)

The safety and effectiveness of XOFLUZA for treatment and post-exposure prophylaxis of influenza in pediatric subjects less than 5 years of age, including neonates, have not been established [see Warnings and Precautions (5.2) and Microbiology (12.4)].

8.5 Geriatric Use

The safety and effectiveness of XOFLUZA in subjects 65 years of age and older has been established and is supported by one randomized, double-blind, controlled trial [see Clinical Studies (14.2)]. In Trial T0832, of 730 XOFLUZA-treated subjects at high risk of influenza-related complications, 209 (29%) subjects were 65 years of age and older. The median time to improvement of influenza symptoms in subjects 65 years of age and older was 70 hours in subjects who received XOFLUZA (N=112) and 88 hours in those who received placebo (N=102). The safety profile observed for this population was similar to that reported in the overall trial population except for nausea, which was reported in 6% of elderly subjects compared to 1% of subjects from 18 to 64 years of age.

10 OVERDOSAGE

Treatment of an overdose of XOFLUZA should consist of general supportive measures, including monitoring of vital signs and observation of the clinical status of the patient. There is no specific antidote for overdose with XOFLUZA.

Baloxavir is unlikely to be significantly removed by dialysis due to high serum protein binding [see Clinical Pharmacology (12.3)].

11 DESCRIPTION

Baloxavir marboxil is an influenza virus PA endonuclease inhibitor.

The active component of XOFLUZA is baloxavir marboxil. The chemical name of baloxavir marboxil is ({(12aR)-12-[(11S)-7,8-Difluoro-6,11-dihydrodibenzo[b,e]thiepin-11-yl]-6,8-dioxo-3,4,6,8,12,12a-hexahydro-1H-[1,4]oxazino[3,4-c]pyrido[2,1-f][1,2,4]triazin-7-yl}oxy)methyl methyl carbonate. The empirical formula of baloxavir marboxil is C27H23F2N3O7S, and the chemical structure is shown below.

Baloxavir marboxil has a molecular mass of 571.55 grams per mole and a partition coefficient (log P) of 2.26. It is freely soluble in dimethylsulfoxide, soluble in acetonitrile, slightly soluble in methanol and ethanol, and practically insoluble in water.

XOFLUZA is supplied as tablets and for oral suspension (in packets and in bottles).

XOFLUZA tablets are white to light yellow, film-coated for oral administration. The 40 mg film-coated tablet contains 40 mg of baloxavir marboxil, and the 80 mg film-coated tablet contains 80 mg of baloxavir marboxil. The inactive ingredients of XOFLUZA tablets are: croscarmellose sodium, hypromellose, lactose monohydrate, microcrystalline cellulose, povidone K25, sodium stearyl fumarate, talc, and titanium dioxide.

XOFLUZA for oral suspension (packets) is supplied as white to light yellow granules in a packet. Each packet contains either 30 mg or 40 mg of baloxavir marboxil. The granules must be reconstituted in about 15 to 20 mL of room temperature drinking water. The inactive ingredients are: hypromellose, maltitol, mannitol, povidone K25, silicon dioxide, sodium chloride, strawberry flavor, sucralose, and talc.

XOFLUZA for oral suspension (bottles) is supplied as white to light yellow granules in an amber glass bottle. Each bottle contains 40 mg (nominal) of baloxavir marboxil. The granules must be reconstituted with 20 mL of drinking water or sterile water to yield a 2 mg/mL greyish white, white to light yellow opaque suspension with strawberry flavor. The inactive ingredients are: hypromellose, maltitol, mannitol, povidone K25, silicon dioxide, sodium chloride, strawberry flavor, sucralose, and talc.

12 CLINICAL PHARMACOLOGY

12.1 Mechanism of Action

Baloxavir marboxil is an antiviral drug with activity against influenza virus [see Microbiology (12.4)].

12.2 Pharmacodynamics

Cardiac Electrophysiology

At twice the expected exposure from recommended dosing, XOFLUZA did not prolong the QTc interval.

Exposure-Response Relationships

In patients 5 years of age and older, when XOFLUZA is dosed by weight as recommended, a flat baloxavir exposure-response (time to alleviation of influenza symptoms) relationship has been observed.

12.3 Pharmacokinetics

Baloxavir marboxil is a prodrug that is almost completely converted to its active metabolite, baloxavir, following oral administration.

Baloxavir pharmacokinetic parameters are presented for healthy adults and adolescents as the mean [% coefficient of variation (%CV)], unless otherwise specified, in Table 5. Absorption, distribution, metabolism, and elimination data for XOFLUZA is presented in Table 6.

Table 5 Pharmacokinetic Parameters of Plasma Baloxavir in Adults and Adolescents (≥ 12 Years of Age)
Pharmacokinetic Parameters of Plasma Baloxavir in Adults and Adolescents [Trial T0831 summary data, mean (%CV)] | XOFLUZA dose 40 mg | XOFLUZA dose 80 mg
AUC (ng∙hr/mL) | 5520 (46.3%) | 6930 (48.6%)
Cmax (ng/mL) | 68.9 (44.9%) | 82.5 (43.0%)
C24 (ng/mL) | 50.9 (45.8%) | 62.6 (45.9%)
C72 (ng/mL) | 24.2 (45.5%) | 30.8 (47.0%)

Table 6 Baloxavir Absorption, Distribution, Metabolism, Elimination Data
Absorption
Tmax (hr) [Median] | 4
Effect of food (relative to fasting) [Meal: approximately 400 to 500 kcal including 150 kcal from fat] | Cmax: ↓48%, AUC0-inf: ↓36%
Distribution
% bound to human serum proteins [in vitro] | 92.9–93.9
Ratio of blood cell to blood | 48.5%–54.4%
Volume of distribution (V/F, L) [Geometric mean (geometric CV%)] | 1180 (20.8%)
Elimination
Clearance (CL/F, L/hr) | 10.3 (22.5%)
Apparent terminal elimination half-life (hr) | 79.1 (22.4%)
Metabolism
Metabolic pathways | Primary: UGT1A3 Secondary: CYP3A4
Excretion
% of dose excreted [Ratio of radioactivity to radio-labeled baloxavir marboxil dose in mass balance study] | Urine: 14.7 (total radioactivity); 3.3 (baloxavir) Feces: 80.1 (total radioactivity)

No clinically significant differences in the pharmacokinetics of baloxavir were observed based on age, sex, presence of risk factors for complicated influenza, creatinine clearance (CrCl: 50 mL/min and above), or moderate hepatic impairment (Child-Pugh class B). The effect of severe renal or hepatic impairment on baloxavir pharmacokinetics has not been evaluated.

Pediatrics (5 to < 12 Years of Age)

Mean (CV%) baloxavir pharmacokinetics in pediatric subjects 5 to < 12 years of age are described in Table 7. Following the approved recommended dosage, baloxavir exposures are similar in pediatric subjects (5 to < 12 years of age) compared to adult and adolescent subjects.

Table 7 Pharmacokinetic Parameters of Plasma Baloxavir in Pediatrics (5 to < 12 Years of Age)
Pharmacokinetic Parameters of Plasma Baloxavir in Pediatrics [Trial CP40563 summary data, mean (%CV); patients not receiving the recommended dose (n=3) were excluded] | XOFLUZA Dose for Subjects Weighing < 20 kg | XOFLUZA Dose for Subjects Weighing ≥ 20 kg
 | (n=8) | (n=55)
 | 2 mg/kg | 40 mg
AUCinf (ng.h/mL) | 5830 (48.5) | 4360 (48.9)
Cmax (ng/mL) | 148 (48.7) | 81.1 (44.0)
Tmax (h) [Median (range)] | 3.5 (2-5.5) | 4.5 (2-23.5)
C24 (ng/mL) | 77.9 (49.2) | 52.4 (43.2)
C72 (ng/mL) | 19.3 (49.7) | 18.0 (50.9)

Body Weight

Baloxavir exposure decreases as body weight increases. No clinically significant difference in exposure was observed between body weight groups in adult and pediatric subjects following the approved recommended dosage.

Race/Ethnicity

Based on a population pharmacokinetic analysis, baloxavir exposure is approximately 35% lower in non-Asians as compared to Asians; this difference is not considered clinically significant when the recommended dose was administered.

Drug Interaction Studies

Clinical Studies

No clinically significant changes in the pharmacokinetics of baloxavir marboxil and its active metabolite, baloxavir, were observed when coadministered with itraconazole (combined strong CYP3A and P-gp inhibitor), probenecid (UGT inhibitor), or oseltamivir.

No clinically significant changes in the pharmacokinetics of the following drugs were observed when coadministered with baloxavir marboxil: midazolam (CYP3A4 substrate), digoxin (P-gp substrate), rosuvastatin (BCRP substrate), or oseltamivir.

Animal Studies

Polyvalent Cations: In monkeys, a 48% to 63% decrease in baloxavir exposure was observed when XOFLUZA was coadministered with calcium, aluminum, magnesium, or iron. No study has been conducted in humans.

In Vitro Studies

Cytochrome P450 (CYP) Enzymes: Both baloxavir marboxil and baloxavir do not inhibit CYP1A2, CYP2B6, CYP2C8, CYP2C9, CYP2C19, or CYP2D6 and do not induce CYP1A2, CYP2B6, or CYP3A4.

Uridine diphosphate (UDP)-glucuronosyl transferase (UGT) Enzymes: Both baloxavir marboxil and baloxavir do not inhibit UGT1A1, UGT1A3, UGT1A4, UGT1A6, UGT1A9, UGT2B7, or UGT2B15.

Transporter Systems: Both baloxavir marboxil and baloxavir are substrates of P-glycoprotein (P-gp). Baloxavir does not inhibit organic anion-transporting polypeptides (OATP) 1B1, OATP1B3, organic cation transporter (OCT) 1, OCT2, organic anion transporter (OAT) 1, OAT3, multidrug and toxin extrusion (MATE) 1, or MATE2K.

12.4 Microbiology

Mechanism of Action

Baloxavir marboxil is a prodrug that is converted by hydrolysis to baloxavir, the active form that exerts anti-influenza virus activity. Baloxavir inhibits the endonuclease activity of the polymerase acidic (PA) protein, an influenza virus-specific enzyme in the viral RNA polymerase complex required for viral gene transcription, resulting in inhibition of influenza virus replication. The 50% inhibitory concentration (IC50) values of baloxavir ranged from 1.4 to 3.1 nM (n=4) for influenza A viruses and 4.5 to 8.9 nM (n=3) for influenza B viruses in a PA endonuclease assay. Viruses with reduced susceptibility to baloxavir have amino acid substitutions in the PA protein.

Antiviral Activity

The antiviral activity of baloxavir against laboratory strains and clinical isolates of influenza A and B viruses was determined in an MDCK cell-based plaque reduction assay. The median 50% effective concentration (EC50) values of baloxavir were 0.73 nM (n=31; range: 0.20–1.85 nM) for subtype A/H1N1 strains, 0.83 nM (n=33; range: 0.35–2.63 nM) for subtype A/H3N2 strains, and 5.97 nM (n=30; range: 2.67–14.23 nM) for type B strains. In an MDCK cell-based virus titer reduction assay, the 90% effective concentration (EC90) values of baloxavir against avian subtypes A/H5N1 and A/H7N9 were in the range of 0.80 to 3.16 nM. The relationship between antiviral activity in cell culture and clinical response to treatment in humans has not been established.

Resistance

Cell Culture

Influenza A virus isolates with reduced susceptibility to baloxavir were selected by serial passage of virus in cell culture in the presence of increasing concentrations of baloxavir. Reduced susceptibility of influenza A virus to baloxavir was conferred by amino acid substitutions I38T (A/H1N1 and A/H3N2), E198K (A/H1N1) and E199G (A/H3N2) in the PA protein of the viral RNA polymerase complex. An E18G (A/H1N1) substitution in the PA protein, selected by a baloxavir analog, also conferred reduced susceptibility to baloxavir.

Clinical Studies

Treatment-emergent substitutions were identified in influenza A and B viruses in clinical studies. Substitutions associated with a >3-fold reduction in susceptibility to baloxavir are shown in Table 8.

Table 8 Treatment-Emergent Amino Acid Substitutions in PA Associated with Reduced Susceptibility to Baloxavir Identified in Clinical Specimens
Influenza Type/Subtype | A/H1N1 | A/H3N2 | B
Amino Acid Substitution | E23G/K/R, A37T, I38F/N/S/T | E23G/K, A37T, I38M/T, E199G | T20K, I38T

Clinical studies in adult and adolescent subjects ≥ 12 years of age:

In adult and adolescent subjects who had a confirmed influenza virus infection, the overall frequencies of treatment-emergent amino acid substitutions associated with reduced susceptibility to baloxavir were 5% (6/134), 11% (53/485), and 1% (2/224) in influenza A/H1N1, A/H3N2, and B virus infections, respectively, in pooled data from Trials T0821, T0831, and T0832 [see Clinical Studies (14)]. In Trial T0834, of 303 subjects ≥ 12 years of age who received XOFLUZA post-exposure prophylaxis, 32 were viral RNA-positive post-baseline, including 17 subjects who were evaluated for resistance. Of these 17 subjects, influenza virus with substitutions associated with reduced susceptibility to baloxavir was identified in 4/4 subjects who developed clinical influenza (as described for the primary endpoint) and 6/13 other subjects evaluated who did not meet the primary endpoint definition for clinical influenza [see Clinical Studies (14)].

Clinical studies in pediatric subjects 5 to < 12 years of age:

Selection of influenza viruses with treatment-emergent amino acid substitutions associated with reduced susceptibility to baloxavir has occurred at higher frequencies in pediatric subjects 5 to <12 years of age compared to subjects ≥ 12 years of age. Such viruses were detected with overall frequencies of 17% (2/12), 18% (17/93), and 0% (0/13) in influenza A/H1N1, A/H3N2, and B virus infections, respectively, in pooled data from 4 pediatric treatment trials in subjects 5 to < 12 years of age.

In Trial T0834, of a subgroup of 57 subjects 5 to < 12 years of age who received XOFLUZA post-exposure prophylaxis, 12 were viral-RNA positive post-baseline, including 10 subjects who were evaluated for resistance. Of these 10 subjects, influenza virus with substitutions associated with reduced susceptibility to baloxavir was identified in 2/2 subjects who developed clinical influenza (as described for the primary endpoint) and 1/8 other subjects who did not meet the primary endpoint definition for clinical influenza [see Clinical Studies (14)].

Clinical studies in pediatrics subjects < 5 years of age:

The highest frequencies of treatment-emergent resistance have been observed in pediatric subjects < 5 years of age. In treatment trials in subjects < 5 years of age, treatment-emergent amino acid substitutions associated with reduced susceptibility to baloxavir occurred in 23% (5/22), 58% (32/55), and 5% (1/19) of influenza A/H1N1, A/H3N2, and B virus infections, respectively, in pooled data from 5 pediatric treatment trials.

Surveillance Studies

Amino acid substitutions associated with reduced susceptibility to baloxavir have also been identified in surveillance studies or in cell culture studies evaluating the impact of resistance substitutions identified in one influenza virus type/subtype on baloxavir susceptibility when introduced into other influenza virus types/subtypes (Table 9).

Table 9 Amino Acid Substitutions in PA Associated with Reduced Susceptibility to Baloxavir Identified in Surveillance and in Cell Culture Resistance Studies
Influenza Type/Subtype | A/H1N1 | A/H3N2 | B
Amino Acid Substitution | A36V [Identified in human surveillance isolates, antiviral treatment unknown] , I38L/M [Known substitution associated with reduced susceptibility to baloxavir identified in clinical specimens or surveillance isolates but evaluated in the indicated alternative type/subtype by reverse genetics] | E23R, A36V, I38F/N/S | I38F/M/N/S

None of the treatment-emergent substitutions associated with reduced susceptibility to baloxavir were identified in virus from pretreatment respiratory specimens in the clinical studies.

Treatment-emergent resistance has been associated with influenza virus rebound and prolonged virus shedding; however, the impact of prolonged shedding on clinical outcomes and virus transmission potential is currently unknown.

The frequency of baloxavir resistance and the prevalence of such resistant virus may vary seasonally and geographically. Prescribers should consider available information from the U.S. CDC and/or a local health department on current influenza virus drug susceptibility patterns and treatment effects when deciding whether to use XOFLUZA.

Cross-Resistance

Cross-resistance between baloxavir and neuraminidase (NA) inhibitors, or between baloxavir and M2 proton pump inhibitors (adamantanes), is not expected because these drugs target different viral proteins. The NA inhibitor oseltamivir is active against viruses with reduced susceptibility to baloxavir, including A/H1N1 virus with PA substitutions E23K or I38F/T; A/H3N2 virus with PA substitutions E23G/K, A37T, I38M/T, or E199G; and type B virus with the PA substitution I38T. Influenza virus may carry amino acid substitutions in PA that reduce susceptibility to baloxavir and at the same time carry resistance-associated substitutions for NA inhibitors and M2 proton pump inhibitors.

Baloxavir is active against NA inhibitor-resistant strains, including A/H1N1 and A/H5N1 viruses with the NA substitution H275Y (A/H1N1 numbering), A/H3N2 virus with the NA substitutions E119V or R292K, A/H7N9 virus with the NA substitution R292K (A/H3N2 numbering), and type B virus with the NA substitutions R152K or D198E (A/H3N2 numbering). The clinical relevance of phenotypic cross-resistance evaluations has not been established.

Immune Response

Interaction studies with influenza vaccines and baloxavir marboxil have not been conducted.

13 NONCLINICAL TOXICOLOGY

13.1 Carcinogenesis, Mutagenesis, Impairment of Fertility

Carcinogenesis

Carcinogenicity studies have not been performed with baloxavir marboxil.

Mutagenesis

Baloxavir marboxil and the active metabolite, baloxavir, were not mutagenic in in vitro and in in vivo genotoxicity assays, which included bacterial mutation assays in S. typhimurium and E. coli, micronucleus tests with cultured mammalian cells, and in the rodent micronucleus assay.

Impairment of Fertility

In a fertility and early embryonic development study in rats, doses of baloxavir marboxil at 20, 200, or 1,000 mg/kg/day were administered to females for 2 weeks before mating, during mating, and until day 7 of pregnancy. Males were dosed for 4 weeks before mating and throughout mating. There were no effects on fertility, mating performance, or early embryonic development at any dose level, resulting in systemic drug exposure (AUC) approximately 5 times the MRHD.

14 CLINICAL STUDIES

14.1 Treatment of Acute Uncomplicated Influenza—Otherwise Healthy Subjects (12 Years of Age and Older)

Two randomized, controlled, double-blinded clinical trials conducted in two different influenza seasons evaluated efficacy and safety of XOFLUZA in otherwise healthy subjects with acute uncomplicated influenza.

In Trial T0821, a placebo-controlled phase 2 dose-finding trial, a single oral dose of XOFLUZA was compared with placebo in 400 adult subjects 20 to 64 years of age in Japan. All subjects in Trial T0821 were Asian, the majority of subjects were male (62%), and the mean age was 38 years. In this trial, among subjects who received XOFLUZA and had influenza virus typed, influenza A/H1N1 was the predominant strain (63%), followed by influenza B (25%), and influenza A/H3N2 (12%).

In Trial T0831 (NCT02954354), a phase 3, randomized, double-blind, active- and placebo-controlled trial, XOFLUZA was studied in 1,436 otherwise healthy adults and adolescents with signs and symptoms of influenza in the U.S. and Japan. Subjects were 12 to 64 years of age and weighed at least 40 kg. Adults aged 20 to 64 years received weight-based XOFLUZA (subjects who weighed 40 to less than 80 kg received 40 mg and subjects who weighed 80 kg and above received 80 mg) (N=612) or placebo as a single oral dose on day 1 (N=310) or oseltamivir twice a day for 5 days (N=514). Subjects in the XOFLUZA and placebo arms received a placebo for the duration of oseltamivir dosing after XOFLUZA or placebo dosing in that arm. Adolescent subjects 12 to less than 20 years of age received weight-based XOFLUZA or placebo as a single oral dose.

Seventy-eight percent of subjects in Trial T0831 were Asian, 17% were White, and 4% were Black or African American. The mean age was 34 years, and 11% of subjects were less than 20 years of age; 54% of subjects were male and 46% female. In Trial T0831, 1,062 of 1,436 enrolled subjects had influenza confirmed by RT-PCR and were included in the efficacy analysis (XOFLUZA N=455, placebo N=230, or oseltamivir N=377). Among subjects who received XOFLUZA and had influenza virus typed, influenza A/H3N2 was the predominant strain (90%), followed by influenza B (9%), and influenza A/H1N1 (2%).

In both Trials T0821 and T0831, eligible subjects had an axillary temperature of at least 38˚C, at least one moderate or severe respiratory symptom (cough, nasal congestion, or sore throat), and at least one moderate or severe systemic symptom (headache, feverishness or chills, muscle or joint pain, or fatigue), and all were treated within 48 hours of symptom onset. Subjects participating in the trial were required to self-assess their influenza symptoms as "none," "mild," "moderate," or "severe" twice daily. The primary efficacy population was defined as those with a positive rapid influenza diagnostic test (Trial T0821) or positive influenza reverse transcription polymerase chain reaction (RT-PCR) (Trial T0831) at trial entry.

The primary endpoint of both trials, time to alleviation of symptoms, was defined as the time when all seven symptoms (cough, sore throat, nasal congestion, headache, feverishness, myalgia, and fatigue) had been assessed by the subject as none or mild for a duration of at least 21.5 hours.

In both trials, XOFLUZA treatment at the recommended dose resulted in a statistically significant shorter time to alleviation of symptoms compared with placebo in the primary efficacy population (Tables 10 and 11).

Table 10 Time to Alleviation of Symptoms After Single Dose in Otherwise Healthy Adults with Acute Uncomplicated Influenza in Trial T0821 (Median Hours)
 | XOFLUZA 40 mg (95% CI [CI: Confidence interval]) N=100 | Placebo (95% CI) N=100
Adults (20 to 64 Years of Age) | 50 hours [XOFLUZA treatment resulted in a statistically significant shorter time to alleviation of symptoms compared to placebo using the Gehan-Breslow's generalized Wilcoxon test (p-value: 0.014, adjusted for multiplicity using the Bonferroni method). The primary analysis using the Cox Proportional Hazards Model did not reach statistical significance (p-value: 0.165).] (45, 64) | 78 hours (68, 89)

Table 11 Time to Alleviation of Symptoms After Single Dose in Otherwise Healthy Subjects 12 Years of Age and Older with Acute Uncomplicated Influenza in Trial T0831 (Median Hours)
 | XOFLUZA 40 mg or 80 mg (95% CI [CI: Confidence interval]) N=455 | Placebo (95% CI) N=230
Subjects (≥ 12 Years of Age) | 54 hours [XOFLUZA treatment resulted in a statistically significant shorter time to alleviation of symptoms compared to placebo using the Peto-Prentice's generalized Wilcoxon test (p-value: < 0.001).] (50, 59) | 80 hours (73, 87)

In Trial T0831, there was no difference in the time to alleviation of symptoms between subjects (age ≥ 20 years) who received XOFLUZA (54 hours) and those who received oseltamivir (54 hours). For adolescent subjects (12 to 17 years of age) in Trial T0831, the median time to alleviation of symptoms for subjects infected with influenza and who received XOFLUZA (N=63) was 54 hours (95% CI of 43, 81) compared to 93 hours (95% CI of 64, 118) in the placebo arm (N=27).

The number of subjects who received XOFLUZA at the recommended dose and who were infected with influenza type B virus was limited, including 24 subjects in Trial T0821 and 38 subjects in Trial T0831. In the influenza B subset in Trial T0821, the median time to alleviation of symptoms in subjects who received 40 mg XOFLUZA was 63 hours (95% CI of 43, 70) compared to 83 hours (95% CI of 58, 93) in subjects who received placebo. In the influenza B subset in Trial T0831, the median time to alleviation of symptoms in subjects who received 40 mg or 80 mg XOFLUZA was 93 hours (95% CI of 53, 135) compared to 77 hours (95% CI of 47, 189) in subjects who received placebo.

14.2 Treatment of Acute Uncomplicated Influenza—High Risk Subjects (12 Years of Age and Older)

Trial T0832 (NCT02949011) was a randomized, double-blind, placebo- and active-controlled trial to evaluate the efficacy and safety of a single oral dose of XOFLUZA compared with placebo or oseltamivir in adult and adolescent subjects 12 years of age or older with influenza who were at high risk of developing influenza-related complications.

A total of 2,182 subjects with signs and symptoms of influenza were randomized to receive a single oral dose of 40 mg or 80 mg of XOFLUZA according to body weight (subjects who weighed 40 to less than 80 kg received 40 mg and subjects who weighed 80 kg and above received 80 mg) (N=729), oseltamivir 75 mg twice daily for 5 days (N=725), or placebo (N=728). Twenty-eight percent of subjects were Asian, 59% were White, and 10% were Black or African American. The mean age was 52 years, and 3% of subjects were less than 18 years of age; 43% of subjects were male and 57% female.

High risk factors were based on the Centers for Disease Control and Prevention definition^1 of health factors known to increase the risk of developing serious complications from influenza. The majority of subjects had underlying asthma or chronic lung disease, diabetes, heart disease, morbid obesity, or were 65 years of age or older.

In Trial T0832, 1,158 of the 2,182 enrolled subjects had influenza confirmed by RT-PCR and were included in the efficacy analysis (XOFLUZA N=385, placebo N=385, or oseltamivir N=388). Among subjects in whom only one type/subtype of influenza virus was identified, 50% were infected with subtype A/H3N2, 43% were infected with type B, and 7% were infected with subtype A/H1N1.

Eligible subjects had an axillary temperature of at least 38°C, at least one moderate or severe respiratory symptom (cough, nasal congestion, or sore throat), and at least one moderate or severe systemic symptom (headache, feverishness or chills, muscle or joint pain, or fatigue), and all were treated within 48 hours of symptom onset. Subjects participating in the trial were required to self-assess their influenza symptoms as "none," "mild," "moderate," or "severe" twice daily. A total of 215 subjects (19%) had preexisting symptoms (cough, muscle or joint pain, or fatigue) associated with their underlying high-risk condition that were worsened due to influenza infection. The primary efficacy endpoint was time to improvement of influenza symptoms (cough, sore throat, headache, nasal congestion, feverishness or chills, muscle or joint pain, and fatigue). This endpoint included alleviation of new symptoms and improvement of any preexisting symptoms that had worsened due to influenza. A statistically significant improvement in the primary endpoint was observed for XOFLUZA when compared with placebo (see Table 12).

Table 12 Time to Improvement of Symptoms After Single Dose in High-Risk Subjects 12 Years of Age and Older with Acute Uncomplicated Influenza in Trial T0832 (Median Hours)
XOFLUZA 40 mg or 80 mg [The dosage of XOFLUZA was based on subject's weight.] (95% CI [CI: Confidence interval]) N=385 | Placebo (95% CI) N=385
73 hours [XOFLUZA treatment resulted in a significant reduction in Time to Improvement of Influenza Symptoms compared to placebo using Peto-Prentice's generalized Wilcoxon test (p-value: < 0.001).] (67, 85) | 102 hours (93, 113)

There was no statistically significant difference in the median time to improvement of influenza symptoms in the subjects who received XOFLUZA (73 hours) and those who received oseltamivir (81 hours). The median time to improvement of influenza symptoms in the limited number of adolescent subjects aged 12 to 17 years infected with influenza virus was similar for subjects who received XOFLUZA (188 hours) or placebo (191 hours) (N=13 and N=12, respectively).

For subjects infected with type B virus, the median time to improvement of influenza symptoms was 75 hours in the XOFLUZA group (95% CI of 67, 90) compared to 101 hours in the placebo group (95% CI of 83, 116).

14.3 Treatment of Acute Uncomplicated Influenza—Otherwise Healthy and High-Risk Pediatric Subjects (5 to < 12 Years of Age)

Trial CP40563 (NCT03629184) was a randomized, double-blind, multicenter, active-controlled trial, designed to evaluate the safety, efficacy, and pharmacokinetics of a single oral dose of XOFLUZA compared with oseltamivir in otherwise healthy pediatric subjects (including subjects aged 5 to < 12 years of age) with influenza-like symptoms. Eligible subjects had a tympanic temperature of at least 38°C and at least one respiratory symptom of either cough or nasal congestion.

A total of 118 subjects 5 to less than 12 years of age were randomized and received a single one-time oral dose of XOFLUZA (N=79) based on body weight (2 mg/kg for subjects weighing < 20 kg or 40 mg for subjects weighing ≥ 20 kg) or oseltamivir (N=39) for 5 days (dose based on body weight). Subjects at high risk of developing complications associated with influenza were included in the trial [16% (19/118)]. The primary objective was to compare the safety of a single one-time dose of XOFLUZA with 5 days of oseltamivir administered twice daily. The secondary efficacy endpoint included time to alleviation of influenza signs and symptoms, which was defined as the time when all of the following were met for at least 21.5 hours: cough and nasal symptoms were assessed by the caregiver as no problem or minor problem, subject was able to return to normal daily activity, and subject was afebrile (temperature ≤ 37.2°C). However, the trial was not powered to detect statistically significant differences in this secondary endpoint.

Of the 118 randomized subjects 5 to less than 12 years of age in Trial CP40563, 94 subjects had influenza confirmed by RT-PCR at baseline or during the trial; 89% percent of subjects were White, 3% Black or African American and 8% Other/unknown/multiple races. The mean age was 8 years [SD=1.97]; 56% of subjects were female and 44% male. The predominant influenza virus strain in this trial was the A/H3N2 subtype (67%), followed by A/H1N1 (20%) and type B (9%).

The median time to alleviation of influenza signs and symptoms was 138 hours in the XOFLUZA arm (95% CI of 117, 163) and 126 hours in the oseltamivir arm (95% CI of 96, 166).

14.4 Post-Exposure Prophylaxis of Influenza (5 Years of Age and Older)

Trial T0834 was a phase 3, randomized, double-blind, multicenter, placebo-controlled trial designed to evaluate the efficacy of a single oral dose of XOFLUZA compared with placebo in the prevention of influenza in subjects who were household contacts of influenza-infected patients in Japan. Influenza-infected index patients were required to have onset of symptoms for ≤ 48 hours, and subjects (household contacts) were required to have lived with the influenza-infected index patient for ≥ 48 hours.

A total of 715 subjects (XOFLUZA N=360, placebo N=355) 5 years of age and older were randomized and received a single oral dose of XOFLUZA according to body weight and age, or placebo, on Day 1. Subjects received a single dose of XOFLUZA according to body weight. The primary efficacy endpoint was the proportion of household subjects who were infected with influenza virus and presented with fever and at least one respiratory symptom from day 1 to day 10. Influenza infection was confirmed by RT-PCR, fever was defined as a body temperature (axillary) ≥ 37.5°C, and respiratory symptoms were defined as having a symptom of "cough" or "nasal discharge/nasal congestion" with a severity of moderate or severe as assessed by the subject.

The mean age of subjects that were ≥ 5 years of age in Trial T0834 was 35 years; 108 (15%) were 5 to < 12 years, 33 (5%) were ≥ 12 to < 18 years of age, 551 (77%) were ≥ 18 to < 65 years of age, and 23 (3%) were ≥ 65 years of age. All subjects were Asian, 80% were female, and 20% were male.

In subjects that were 5 years of age and older, there was a statistically significant reduction in the proportion of household contacts (subjects) with laboratory-confirmed clinical influenza from 13% in the placebo group to 2% in the XOFLUZA group (see Table 13).

Table 13 Proportion of Household Contacts (Subjects 5 Years of Age and Older) Infected with Influenza Virus with Fever and at Least One Respiratory Symptom (Trial T0834)
XOFLUZA (95% CI [CI: Confidence interval (%) XOFLUZA treatment resulted in a significant reduction in the risk ratio of patients who were infected with influenza virus and presented with fever compared to placebo using modified Poisson regression for a binary response (p-value: < 0.0001).]) N=360 | Placebo (95% CI) N=355
6 (2%) | 47 (13%)
(1%, 4%) | (10%, 17%)

In the 108 pediatric subjects 5 to less than 12 years of age enrolled in Trial T0834, 57 subjects received XOFLUZA and 51 received placebo. In this age group, the proportion of subjects with laboratory-confirmed clinical influenza was 4% in the XOFLUZA group and 14% in the placebo group.

15 REFERENCES

1. "People at High-Risk for Flu Complications." Refer to U.S. Centers for Disease Control and Prevention "Influenza (Flu)" website.

16 HOW SUPPLIED/STORAGE AND HANDLING

XOFLUZA is supplied as tablets (40 mg and 80 mg), granules (30 mg and 40 mg) that are reconstituted into a for oral suspension (packets) and as granules that are reconstituted into a for oral suspension (bottles) [40 mg/20 mL (2 mg/mL)] . The single oral dose to be administered depends on body weight [see Dosage and Administration (2.2)].

XOFLUZA Tablets

How Supplied

- 40 mg white to light yellow, oblong-shaped, film-coated tablets debossed with "BXM40" on one side available as:
  - 1 × 40 mg tablet per blister card in secondary packaging: NDC 50242-860-01
- 80 mg white to light yellow, oblong shaped, film-coated tablets debossed with "BXM80" on one side available as:
  - 1 × 80 mg tablet per blister card in secondary packaging: NDC 50242-877-01

STORAGE AND HANDLING

Storage: Store tablets in their blister package at 20°C to 25°C (68°F to 77°F); excursions are permitted between 15°C and 30°C (59°F to 86°F) [see USP Controlled Room Temperature].

XOFLUZA for Oral Suspension (Packets)

How Supplied: XOFLUZA for oral suspension (packets) are supplied as granules that are white to light yellow in packets. The granules are reconstituted in about 15 to 20 mL of room temperature drinking water to form an oral suspension. Each carton contains 1 packet available as:

- 1 × 30 mg packet: NDC 50242-599-01
- 1 × 40 mg packet: NDC 50242-617-01

There is no preservative.

Storage: Store granules (packets) at 20°C to 25°C (68°F to 77°F) and keep in the original package; excursions are permitted between 15°C and 30°C (59°F and 86°F) [see USP Controlled Room Temperature].

XOFLUZA for Oral Suspension (Bottles)

How Supplied: XOFLUZA for oral suspension, 40 mg/20 mL (2 mg/mL) are supplied as white to light yellow granules in an amber glass bottle with a child-resistant cap. When reconstituted with drinking water or sterile water, the usable volume of the for oral suspension is 20 mL, equivalent to 40 mg of baloxavir marboxil. XOFLUZA for oral suspension is available as:

- 40 mg/20 mL (2 mg/mL) for oral suspension: NDC 50242-583-01

There is no preservative. Must administer within 10 hours after reconstitution.

STORAGE AND HANDLING

Storage: Store granules (bottles) at 20°C to 25°C (68°F to 77°F) and keep in the original bottle; excursions are permitted between 15°C and 30°C (59°F and 86°F) [see USP Controlled Room Temperature].

Store reconstituted suspension no longer than 10 hours at 20°C to 25°C (68°F to 77°F) when reconstituted with drinking water or sterile water. The suspension must be discarded if not used within 10 hours of preparation or if suspension has been stored above 25°C (77°F).

17 PATIENT COUNSELING INFORMATION

Advise the patient to read the FDA-approved patient labeling (Patient Information).

Important Dosing Information

Instruct patients to begin treatment with XOFLUZA as soon as possible at the first appearance of influenza symptoms, within 48 hours of onset of symptoms. Instruct patients to start taking XOFLUZA for prevention as soon as possible after exposure [see Dosage and Administration (2.2)].

XOFLUZA can be taken with or without food, but advise patients not to take with dairy products, calcium-fortified beverages, polyvalent cation-containing laxatives, antacids, or oral supplements (e.g., calcium, iron, magnesium, selenium, or zinc) [see Dosage and Administration (2.2) and Drug Interactions (7.1)].

Advise patients to follow the healthcare provider's dosing recommendation for a single, one-time dose of XOFLUZA. XOFLUZA is dosed based on weight and is available as tablets, and for oral suspension (packets and bottles). XOFLUZA for oral suspension in a packet is not made into a suspension but rather mixed with a small amount of room temperature drinking water to aid administration.

Tablets: Provided as a blister card containing either one tablet of 40 mg, or one tablet of 80 mg as a single dose [see Dosage and Administration (2.2)].

For Oral Suspension:

- Provided in a packet containing either 30 mg or 40 mg baloxavir marboxil. Advise patients or caregivers to read and follow the Instructions for Use for details on the preparation and administration (oral or via enteral feeding tube). XOFLUZA for oral suspension (packets) should be taken immediately after mixing and fully dispersing with water because the product does not contain a preservative [see Dosage and Administration (2.2, 2.3), and How Supplied/Storage and Handling (16)].
- Provided in a bottle containing 40 mg/20 mL (2 mg/mL) after reconstitution by the healthcare provider. Advise the patients and/or caregiver to use a measuring device (oral syringe) to measure their prescribed dose. Counsel patients and/or caregivers how to use the measuring device (oral syringe) provided and inform patients that they may need to draw up XOFLUZA for oral suspension (bottles) multiple times using the oral syringe to receive the full dosage. The suspension should be taken as soon as possible but no later than 10 hours after reconstitution by the healthcare provider because the product does not contain a preservative [see Dosage and Administration (2.2, 2.4), and How Supplied/Storage and Handling (16)].

Hypersensitivity

Advise patients and/or caregivers of the risk of severe allergic reactions such as anaphylaxis, angioedema, urticaria, and erythema multiforme. Instruct patients and/or caregivers to seek immediate medical attention if an allergic-like reaction occurs or is suspected [see Contraindications (4) and Warnings and Precautions (5.1)].

Influenza Vaccines

Because of the potential for antivirals to decrease the effectiveness of live attenuated influenza vaccines, advise patients to consult their healthcare provider prior to receiving a live attenuated influenza vaccine after taking XOFLUZA [see Drug Interactions (7.2)].

Distributed by:
Genentech USA, Inc.
A Member of the Roche Group
1 DNA Way
South San Francisco, CA 94080-4990

XOFLUZA® is a registered trademark of Genentech, Inc.
© 2025 Genentech USA, Inc.

PATIENT INFORMATION

XOFLUZA® (zoh-FLEW-zuh)
(baloxavir marboxil)
tablets

XOFLUZA® (zoh-FLEW-zuh)
(baloxavir marboxil)
for oral suspension

What is XOFLUZA?
XOFLUZA is a prescription medicine used to:

- treat the flu (influenza) in people 5 years of age and older who have flu symptoms for no more than 48 hours and who are:
  - otherwise healthy or
  - at high risk of developing problems from the flu.
- prevent the flu in people 5 years of age and older following contact with a person who has the flu (post-exposure prophylaxis).

XOFLUZA does not treat or prevent illness that is caused by infections other than the influenza virus.
XOFLUZA does not prevent bacterial infections that may happen with the flu.
It is not known if XOFLUZA is safe and effective for the treatment and prevention of the flu in children less than 5 years of age. XOFLUZA is not for use in children less than 5 years of age.

Do not take XOFLUZA if you are allergic to baloxavir marboxil or any of the ingredients in XOFLUZA. See the end of this leaflet for a complete list of ingredients in XOFLUZA.

Before you take XOFLUZA, tell your healthcare provider about all of your medical conditions, including if you:

- are pregnant or plan to become pregnant. It is not known if XOFLUZA can harm your unborn baby.
- are breastfeeding or plan to breastfeed. It is not known if XOFLUZA passes into your breast milk.

Talk to your healthcare provider before you receive a live flu vaccine after taking XOFLUZA.
Tell your healthcare provider about all the medicines you take, including prescription and over-the-counter medicines, vitamins, and herbal supplements.
Know the medicines you take. Keep a list of them to show your healthcare provider and pharmacist when you get a new medicine.

How should I take or give XOFLUZA?

- Take or give XOFLUZA exactly as directed by your healthcare provider or pharmacist.
- Your healthcare provider will prescribe XOFLUZA as a single, one-time dose.
- Your healthcare provider will prescribe XOFLUZA tablets, or XOFLUZA oral suspension packets or XOFLUZA oral suspension bottles (provided with an oral syringe).
- Your healthcare provider will prescribe XOFLUZA based on your or your child's weight.
- XOFLUZA may be given through a feeding tube that is 4 French or larger. Follow your healthcare provider's instructions for giving XOFLUZA through a feeding tube. Take XOFLUZA with or without food.
- Do not take XOFLUZA with dairy products, calcium-fortified beverages, laxatives, antacids or oral supplements containing calcium, iron, magnesium, selenium, or zinc.
- If you take too much XOFLUZA, go to the nearest emergency room right away.

If your healthcare provider prescribes you XOFLUZA for oral suspension (packets):

- See the detailed Instructions for Use for information about how to prepare and take or give a dose of XOFLUZA for oral suspension (packets).
- Your or your child's total prescribed dose of XOFLUZA for oral suspension (packets) may require preparing one or two packets of XOFLUZA.
- Disperse the oral granules from the XOFLUZA for oral suspension packets into a small container with 1 tablespoon (about 15 to 20 mL) of room temperature drinking water, and take or give the medicine right away.
- Contact your healthcare provider or pharmacist if you have any questions on how to take or give the prescribed dose of XOFLUZA for oral suspension (packets).

If your healthcare provider prescribes you XOFLUZA for oral suspension (bottles):

- The pharmacist will prepare XOFLUZA for oral suspension in a bottle and provide you with an oral syringe. If XOFLUZA is not given to you as a liquid medicine or an oral syringe was not provided, contact your pharmacist.
- Take XOFLUZA before the expiration time and date written by the pharmacist on the bottle label. Do not take XOFLUZA if the expiration time and date have passed. Throw away (discard) the bottle and contact your healthcare provider.
- Your or your child's prescribed dose of XOFLUZA for oral suspension may require less than one bottle, one bottle, or two bottles of XOFLUZA.
- The total prescribed dose of XOFLUZA for oral suspension may require more than one withdrawal from the bottle with the oral syringe.
- Contact your healthcare provider or pharmacist if you have any questions on how to take or give the prescribed dose of XOFLUZA for oral suspension (bottles).

Taking or giving a dose of XOFLUZA for oral suspension (bottles):
Step 1. Swirl the XOFLUZA for oral suspension bottle well before each use. Do not shake.
Step 2. Open the bottle by pushing downward on the child resistant bottle cap and twisting it in the direction of the arrow.
Step 3. Measure the XOFLUZA for oral suspension with the oral syringe provided by the pharmacist to be sure you give the prescribed dose. If the prescribed dose requires more than one withdrawal from the bottle, repeat Steps 3 and 4 for each withdrawal until you take or give the full prescribed dose.
Step 4. Take or give the full contents of the oral syringe.
Step 5. Close the bottle. Throw away any remaining XOFLUZA for oral suspension and the oral syringe.

What are the possible side effects of XOFLUZA?
XOFLUZA may cause serious side effects, including:

- Allergic reactions. Get emergency medical help right away if you develop any of these signs or symptoms of an allergic reaction:

- trouble breathing
- skin rash, hives or blisters

- swelling of your face, throat or mouth
- dizziness or lightheadedness

The most common side effects of XOFLUZA for treatment of the flu in adults and adolescents (12 years of age and older) include:

- diarrhea
- bronchitis
- nausea

- sinusitis
- headache

The most common side effects of XOFLUZA for treatment of the flu in children (5 years of age to less than 12 years of age) include:

- vomiting

- diarrhea

XOFLUZA is not effective in treating or preventing infections other than influenza. Other kinds of infections can appear like flu or occur along with flu and may need different kinds of treatment.
Tell your healthcare provider if you feel worse or develop new symptoms during or after treatment with XOFLUZA or if your flu symptoms do not start to get better.
These are not all the possible side effects of XOFLUZA.
Call your doctor for medical advice about side effects. You may report side effects to FDA at 1-800-FDA-1088.

How should I store XOFLUZA?
XOFLUZA tablets:

- Store XOFLUZA tablets at 68°F to 77°F (20°C to 25°C).
- Store XOFLUZA tablets in the blister package that it comes in.

XOFLUZA for oral suspension (packets):

- Store XOFLUZA for oral suspension at 68°F to 77°F (20°C to 25°C).
- Keep XOFLUZA for oral suspension in the original package.
- XOFLUZA for oral suspension in packets has no preservative.

XOFLUZA for oral suspension (bottles):

- Store XOFLUZA for oral suspension at 68°F to 77°F (20°C to 25°C). Keep XOFLUZA for oral suspension in the original bottle.
- XOFLUZA for oral suspension in a bottle has no preservative.
- Use XOFLUZA for oral suspension by the expiration time and date written on the bottle label. Throw away any XOFLUZA for oral suspension not used by the time and date on the bottle label, or if it has been stored at a temperature above 77°F (25°C).
- XOFLUZA for oral suspension comes in a bottle with a child-resistant cap.

Keep XOFLUZA and all medicines out of the reach of children.

General information about the safe and effective use of XOFLUZA.
Medicines are sometimes prescribed for purposes other than those listed in a Patient Information leaflet. Do not use XOFLUZA for a condition for which it was not prescribed. Do not give XOFLUZA to other people, even if they have the same symptoms that you have. It may harm them. You can ask pharmacist or your healthcare provider for information about XOFLUZA that is written for health professionals.

What are the ingredients in XOFLUZA?
Active ingredient: baloxavir marboxil
XOFLUZA tablets inactive ingredients: croscarmellose sodium, hypromellose, lactose monohydrate, microcrystalline cellulose, povidone K25, sodium stearyl fumarate, talc and titanium dioxide.
XOFLUZA for oral suspension (packets and bottles) inactive ingredients: hypromellose, maltitol, mannitol, povidone K25, silicon dioxide, sodium chloride, strawberry flavor, sucralose, and talc.
Distributed by: Genentech USA, Inc., A Member of the Roche Group, 1 DNA Way, South San Francisco, CA 94080-4990
XOFLUZA® is a registered trademark of Genentech, Inc. © 2025 Genentech USA, Inc.
For more information, go to www.XOFLUZA.com or call 1-855-XOFLUZA (1-855-963-5892).

This Patient Information has been approved by the U.S. Food and Drug Administration.

Revised: 05/2025

INSTRUCTIONS FOR USE
XOFLUZA® (zoh-FLEW-zuh)
(baloxavir marboxil)
for oral suspension

This Instruction for Use contains information on how to prepare and take or give XOFLUZA for oral suspension in packets.

Read these Instructions for Use before preparing and taking or giving XOFLUZA for oral suspension. These Instructions for Use do not take the place of talking to your or your child's healthcare provider about your or your child's medical condition or treatment.

Important information you need to know before preparing and taking or giving XOFLUZA for oral suspension

- XOFLUZA is prescribed as a single, one-time dose.
- Wash your hands before and after preparing, taking, or giving XOFLUZA for oral suspension.
- XOFLUZA for oral suspension packets must be mixed with 1 tablespoon (about 15 to 20 mL) of room temperature drinking water.
- Take or give XOFLUZA for oral suspension right away after mixing.
- Check the expiration date and the product for damage before use. Do not use if expired or damaged.
- If you are prescribed the 80 mg dose of XOFLUZA for oral suspension, you will need to take two packets of 40 mg XOFLUZA, one at a time, until your full prescribed dose is taken.
- XOFLUZA for oral suspension can be taken by mouth or given through a feeding tube. Follow your healthcare provider's instructions for giving XOFLUZA through a feeding tube.

Your healthcare provider will prescribe XOFLUZA packets based on your or your child's weight. See the dosing chart below for the prescribed dose and number of XOFLUZA packets needed based on your or your child's weight.

Body weight | Prescribed dose and number of XOFLUZA packets needed
33 lbs (15 kg) to less than 44 lbs (20 kg) | 30 mg (One 30 mg packet)
44 lbs (20 kg) to less than 176 lbs (80 kg) | 40 mg (One 40 mg packet)
At least 176 lbs (80 kg) and above | 80 mg (two 40 mg packets)

Supplies needed to prepare and take or give XOFLUZA for oral suspension:

- your prescribed dose of XOFLUZA packets
- a tablespoon (about 15 to 20 mL) of room temperature drinking water in a container
- an enteral syringe (if giving XOFLUZA for oral suspension through a feeding tube).

Preparing XOFLUZA for oral suspension

Step 1. Wash and dry your hands.

Step 2: Check your dose
Your healthcare provider will prescribe:

- One 30 mg packet, or
- One 40 mg packet, or
- Two 40 mg packets for a dose of 80 mg.

For the 80 mg dose, you will use two 40 mg packets. Take the packets separately. Follow steps 3 to 7 to take the first packet, then repeat steps 3 to 7 to take the second packet.

Step 3. Tap the packet to make sure the granules are on one side of the packet.
Open the packet by hand or with scissors. (Figure A)
Do not cut the granules with the scissor.

Figure A

Step 4. Add the granules to a small container containing 1 tablespoon (about 15 to 20 mL) of room temperature drinking water. (Figure B)
Tap the packet to make sure all granules have been removed.

Figure B

Step 5. Gently swirl the cup for 1 minute, or until the granules have fully dispersed. (Figure C)
Go to Step 6 for taking XOFLUZA for oral suspension by mouth, or
Go to Step 10 for giving XOFLUZA for oral suspension through a feeding tube.

Figure C

Taking XOFLUZA for oral suspension by mouth

Step 6. Drink the mixture right away. (Figure D)

Figure D

Step 7. Refill the container with 1 tablespoon (about 15 to 20 mL) of drinking water and swirl to get any remaining granules. (Figure E)
Drink right away.
Repeat this step one more time if there are still granules left in the container.
If your prescribed dose requires two XOFLUZA packets, repeat Steps 2 through 7.

Figure E

Step 8. Wash your hands and all supplies used to take XOFLUZA for oral suspension. (Figure F)

Figure F

Step 9. Throw away the empty packet and clean the container with soap and water.

Giving XOFLUZA for oral suspension through a feeding tube

- To take or give XOFLUZA for oral suspension through a feeding tube, review the manufacturer's instructions and consult your healthcare provider.
- Give XOFLUZA for oral suspension through a tube that is 4 French or larger.
- Follow Steps 2 through 5 to prepare XOFLUZA for oral suspension.
- Flush the feeding tube with 1 mL of water before and after feeding tube administration.

Step 10
Place the enteral syringe tip right away into the container and slowly pull up the plunger to draw up all the oral suspension. (Figure G)
Do not wait to draw up the oral suspension. If the mixture sits for too long, it may settle to the bottom, and you may not get the full dose.

Figure G

Step 11
Place the enteral syringe tip into the feeding tube. Slowly push the plunger all the way down to give XOFLUZA. (Figure H)

Figure H

Step 12
Refill the container with 1 tablespoon (about 15 to 20 mL) of drinking water and swirl to get any remaining granules left in the container. (Figure I) Use this water to flush the feeding tube.
Repeat this step one more time if there are still granules left in the container.
If your prescribed dose requires 2 XOFLUZA packets, repeat Steps 2 through 5 to prepare the XOFLUZA for oral suspension, then repeat Steps 10 through 12.

Figure I

Step 13
Wash your hands with soap and water. Follow the manufacturer's instructions to clean your enteral syringe.

Storing XOFLUZA for oral suspension in packets

- Store XOFLUZA for oral suspension at 68°F to 77°F (20°C to 25°C).
- Keep XOFLUZA for oral suspension in the original package.
- XOFLUZA for oral suspension in packets has no preservative.
- Keep XOFLUZA and all medicines out of reach of children.

Distributed by:
Genentech USA, Inc., A Member of the Roche Group
1 DNA Way, South San Francisco, CA 94080-4990
XOFLUZA® is a registered trademark of Genentech, Inc.
©2025 Genentech USA, Inc.
This Instructions for Use has been approved by the U.S. Food and Drug Administration.
Issued: 05/2025

Representative sample of labeling (see the HOW SUPPLIED section for complete listing):

PRINCIPAL DISPLAY PANEL - 40 mg/20 mL Bottle Carton

NDC 50242-583-01

Xofluza®
(baloxavir marboxil)
for oral suspension

40 mg/20 mL (2 mg/mL)

Each mL contains
2 mg baloxavir marboxil
after constitution.

Take volume prescribed as a
single one-time dose.
Discard unused portion.

Use the appropriate
measuring device for your
total prescribed dose.

Take before the suspension
expires (see bottle label).

No preservative.

20 mL total usable volume
after constitution

Rx only
Genentech

11000080

PRINCIPAL DISPLAY PANEL - 40 mg Tablet Blister Pack Carton

Xofluza®
(baloxavir marboxil) tablet
40 mg per tablet

NDC 50242-860-01

Contains 40 mg total dose (1 x 40 mg tablet)

Usual dosage:
Take the tablet in this package as a single, one-time dose

Rx only

Genentech

11006600

PRINCIPAL DISPLAY PANEL - 80 mg Tablet Blister Pack Carton

Xofluza®
(baloxavir marboxil) tablet
80 mg per tablet

NDC 50242-877-01

Contains 80 mg total dose (1 x 80 mg tablet)

Usual dosage:
Take the tablet in this package as a single, one-time dose

Rx only

Genentech

11006589

PRINCIPAL DISPLAY PANEL - 30 mg Packet Carton

NDC 50242-599-01

Xofluza®
(baloxavir marboxil)
for oral suspension

30 mg per packet

Refer to Instructions for Use inside the carton.

1 packet

Rx only

Genentech

11024214

PRINCIPAL DISPLAY PANEL - 40 mg Packet Carton

NDC 50242-617-01

Xofluza®
(baloxavir marboxil)
for oral suspension

40 mg per packet

Refer to Instructions for Use inside the carton.

1 packet

Rx only

Genentech

11024205